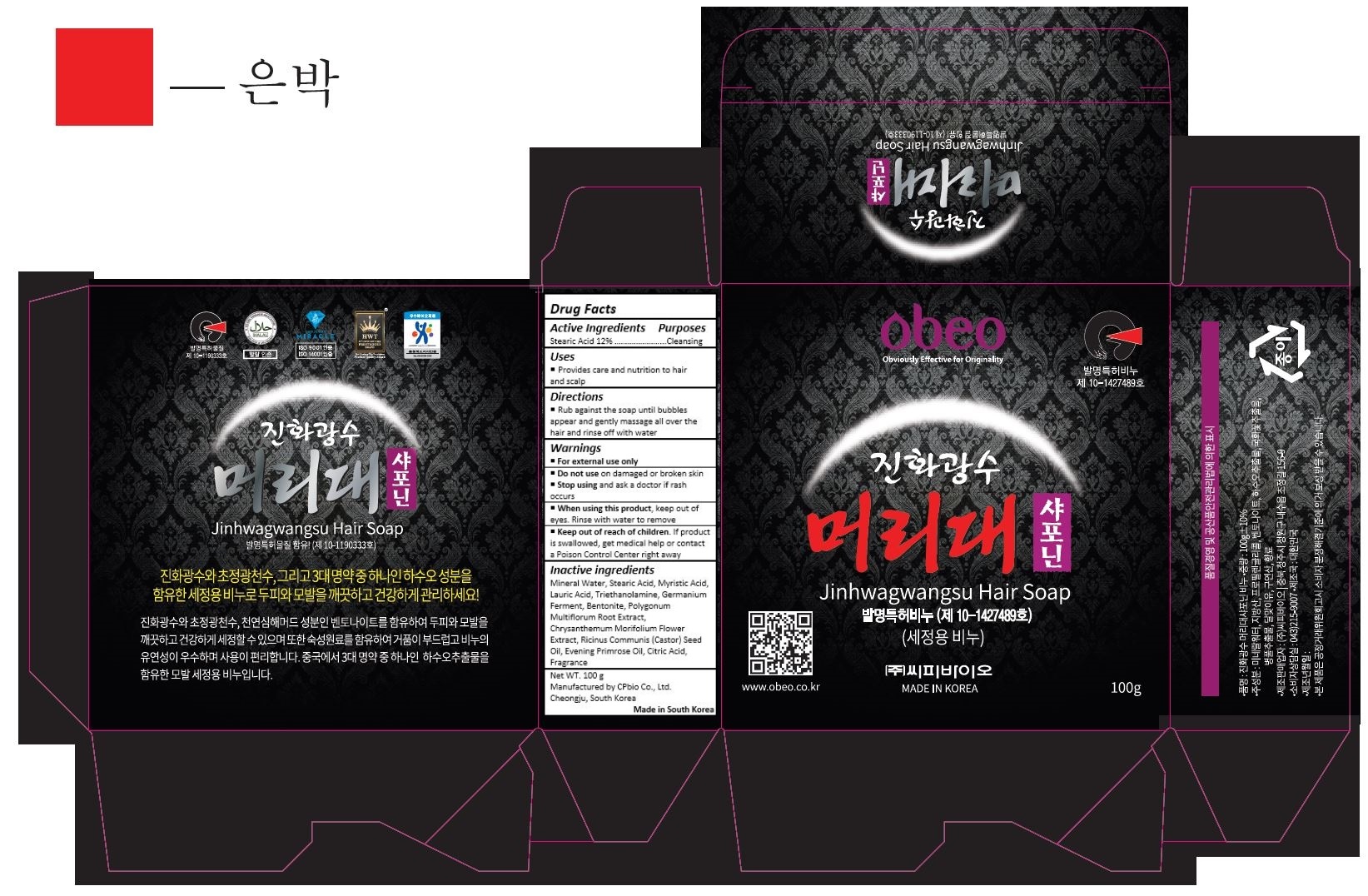 DRUG LABEL: Jinhwagwangsu Hair
NDC: 69871-004 | Form: SOAP
Manufacturer: CPbio Co., Ltd
Category: otc | Type: HUMAN OTC DRUG LABEL
Date: 20160125

ACTIVE INGREDIENTS: STEARIC ACID 12 g/100 g
INACTIVE INGREDIENTS: MYRISTIC ACID; LAURIC ACID; TROLAMINE; PROPYLENE GLYCOL; BENTONITE; FALLOPIA MULTIFLORA ROOT; CHRYSANTHEMUM X MORIFOLIUM FLOWER; CASTOR OIL; EVENING PRIMROSE OIL; CITRIC ACID MONOHYDRATE

Drug Facts

ACTIVE INGREDIENT

Stearic Acid 12%

PURPOSE

Cleansing

INDICATIONS AND USAGE

Provides care and nutrition to hair and scalp

DOSAGE AND ADMINISTRATION

Rub against the soap until bubbles appear and gently massage all over the hair and rinse off with water

WARNINGS

For external use only

Do not use on damaged or broken skin

Stop using and ask a doctor if rash occurs

When using this product, keep out of eyes. Rinse with water to remove

Keep out of reach of children. If product is swallowed, get medical help or contact a Poison Control Center right away.

INACTIVE INGREDIENT

Mineral Water, Stearic Acid, Myristic Acid, Lauric Acid, Triethanolamine, Germanium Ferment, Bentonite, Polygonum Multiflorum Root Extract, Chrysanthemum Morifolium Flower Extract, Ricinus Communis (Castor) Seed Oil, Evening Primrose Oil, Citric Acid, Fragrance